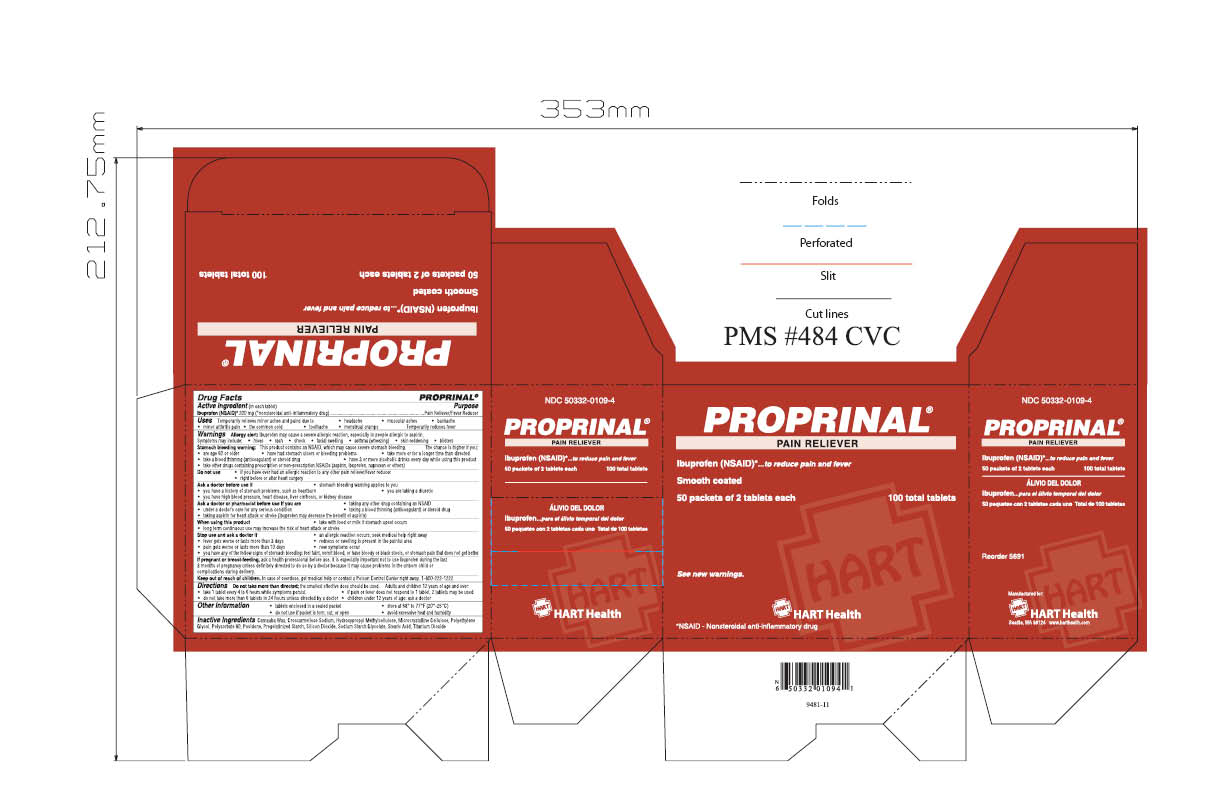 DRUG LABEL: Proprinal
NDC: 50332-0109 | Form: TABLET, SUGAR COATED
Manufacturer: NorMed
Category: otc | Type: HUMAN OTC DRUG LABEL
Date: 20120619

ACTIVE INGREDIENTS: ibuprofen 200 mg/1 1
INACTIVE INGREDIENTS: CROSCARMELLOSE SODIUM; CELLULOSE, MICROCRYSTALLINE; POLYETHYLENE GLYCOLS; POLYSORBATE 80; POVIDONE; SILICON DIOXIDE; STEARIC ACID; TITANIUM DIOXIDE

Proprinal

Active Ingredient (in each tablet)

Ibuprofen (NSAID)* 200mg (*nonsteroidal anti-inflammatory drug)...Pain Reliever/Fever Reducer

INDICATIONS AND USAGE

Temporarily relieves minor aches and pains due to:

- headache
- muscular aches
- backache
- minor arthritis pain
- the common cold
- toothache
- menstrual cramps

Temporarily reduces fever

Allergy alert: Ibuprofen may cause a severe allergic reaction, especially in people allergic to aspirin. Symptoms may include:

- hives
- rash
- shock
- facial swelling
- asthma (wheezing)
- skin reddening
- blisters

Stomach bleeding warning: This product contains an NSAID, which may cause severe stomach bleeding. The chance is higher if you:

- are age 60 or older
- have had stomach ulcers or bleeding problems
- take more or for a longer time than directed
- take a blood thinning (anticoagulant) or steroid drug
- have 3 or more alcohol drinks every day while using this product
- take other drugs containing prescription or non-prescription NSAIDs (aspirin, ibuprofen, naproxen, or others)

Do not use

- if you have ever had an allergic reaction to any other pain reliever/fever reducer
- right before or after heart surgery

Ask a doctor before use if

- stomach bleeding warning applies to you
- you have a history of stomach problems, such as heartburn
- you are taking a diuretic
- you have high blood pressure, heart disease, liver cirrhosis, or kidney disease

Ask a doctor or pharmacist if you are

- unders a doctor's care for any serious condition
- taking any other drug containing an NSAID
- taking a blood thinning (anticoagulant) or steroid drug
- taking aspirin for heart attack or stroke (ibuprofen may decrease the benefit of aspirin)

When using this product

- take with food or milk if stomach upset occurs
- long term continuous use may increase the risk of heart attack or stroke

Stop use and ask a doctor if

- an allergic reaction occurs, seek medical help right away
- fever gets worse or lasts more than 3 days
- pain gets worse or lasts more than 10 days
- redness or swelling is present in the painful area.
- new symptoms occur
- you have any of the following signs of stomach bleeding: feel faint, vomit blood, have bloody or black stools, or stomach pain that does not get better

PREGNANCY OR BREAST FEEDING

If pregnant or breast-feeding, ask a health professional before use. It is especially important not to use ibuprofen during the last 3 months of pregnancy unless definitely directed to do so by a doctor because it may cause problems in the unborn child or complications during delivery.

Keep out of reach of children. In case of overdose, get medical help or contact a Poison Control Center right away. 1-800-222-1222

DOSAGE AND ADMINISTRATION

Directions: do not take more than directed; the smallest effective dose should be used. Adults and children 12 years of age and over:

- take 1 tablet every 4 to 6 hours while symptoms persist
- if pain or fever does not respond to 1 tablet, 2 tablets may be used
- do not take more than 6 tablets in 24 hours unless directed by a doctor

children under 12 years of age: ask a doctor

PURPOSE

Ibuprofen...to reduce pain and fever

Inactive ingredients:

Carnauba Wax, Croscarmellose Sodium, Hydroxypropyl Methylcellulose, Microcrystalline Cellulose, Polyethylene Glycol, Polysorbate 80, Povidone, Pregelatinized Starch, Silicon Dioxide, Sodium Starch Clycolate, Stearic Acid, Titanium Dioxide